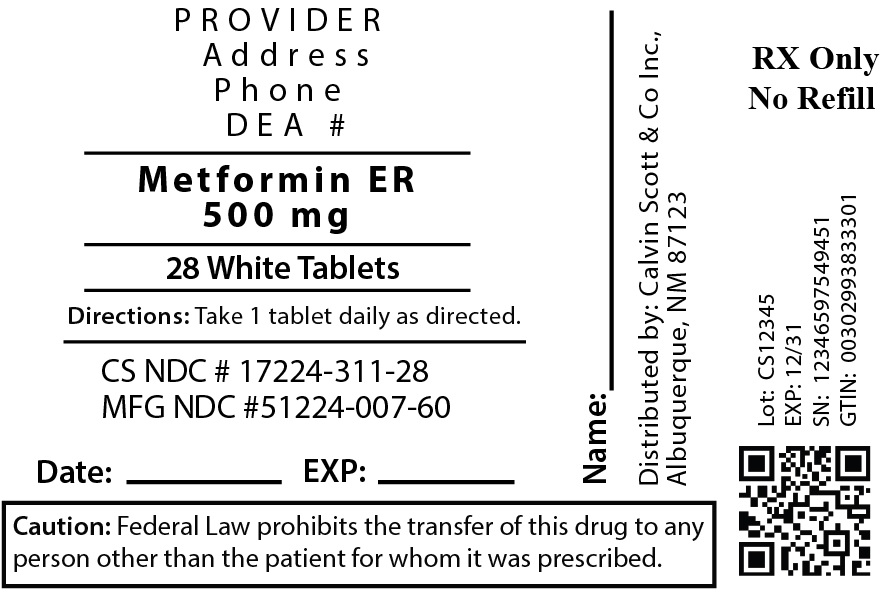 DRUG LABEL: Metformin Hydrochloride Extended-Release 500mg
NDC: 17224-311 | Form: TABLET, EXTENDED RELEASE
Manufacturer: Calvin Scott & Co., Inc.
Category: prescription | Type: HUMAN PRESCRIPTION DRUG LABEL
Date: 20230207

ACTIVE INGREDIENTS: METFORMIN HYDROCHLORIDE 500 mg/1 1
INACTIVE INGREDIENTS: COPOVIDONE K25-31; CARBOXYMETHYLCELLULOSE SODIUM, UNSPECIFIED FORM; HYPROMELLOSE, UNSPECIFIED; MICROCRYSTALLINE CELLULOSE; MAGNESIUM STEARATE

Metformin Hydrochloride Extended-Release Tablets 500mg

HOW TO USE THIS INFORMATION: This is a summary and does NOT have all possible information about this product. This information does not assure that this product is safe, effective, or appropriate for you. This information is not individual medical advice and does not substitute for the advice of your health care professional. Always ask your health care professional for complete information about this product and your specific health needs.

METFORMIN SUSTAINED-ACTION TABLET - ORAL (met-FOR-min)
COMMON BRAND NAME(S): Fortamet, Glucophage XR, Glumetza

WARNING:

Metformin can rarely cause a serious (sometimes fatal) condition called lactic acidosis. Stop taking metformin and get medical help right away if you develop any of the following symptoms of lactic acidosis: unusual tiredness, dizziness, severe drowsiness, chills, blue/cold skin, muscle pain, fast/difficult breathing, slow/irregular heartbeat, stomach pain with nausea, vomiting, or diarrhea. Lactic acidosis is more likely to occur in patients who have certain medical conditions, including kidney or liver disease, recent surgery, a serious infection, conditions that may cause a low level of oxygen in the blood or poor circulation (such as congestive heart failure, recent heart attack, recent stroke), heavy alcohol use, a severe loss of body fluids (dehydration), or X-ray or scanning procedures that require an injectable iodinated contrast drug. Tell your doctor immediately if any of these conditions occur or if you notice a big change in your overall health. You may need to stop taking this medication temporarily. The elderly are also at higher risk, especially those older than 80 years who have not had kidney tests. (See also Side Effects and Precautions sections.)

USES:

Metformin is used with a proper diet and exercise program and possibly with other medications to control high blood sugar. It is used in patients with type 2 diabetes (non-insulin-dependent diabetes). Controlling high blood sugar helps prevent kidney damage, blindness, nerve problems, loss of limbs, and sexual function problems. Proper control of diabetes may also lessen your risk of a heart attack or stroke. Metformin works by helping to restore your body's proper response to the insulin you naturally produce. It also decreases the amount of sugar that your liver makes and that your stomach/intestines absorb.

OTHER USES:

This section contains uses of this drug that are not listed in the approved professional labeling for the drug but that may be prescribed by your health care professional. Use this drug for a condition that is listed in this section only if it has been so prescribed by your health care professional. Metformin may be used with lifestyle changes such as diet and exercise to prevent diabetes in people who are at high risk for becoming diabetic. It is also used in women with a certain disease of the ovaries (polycystic ovarian syndrome). Metformin may make menstrual cycles more regular and increase fertility.

HOW TO USE:

Read the Patient Information Leaflet if available from your pharmacist before you start taking metformin and each time you get a refill. If you have any questions, consult your doctor or pharmacist. Take this medication by mouth as directed by your doctor, usually once daily with the evening meal. Drink plenty of fluids while taking this medication unless otherwise directed by your doctor. Do not crush or chew this medication. Doing so can release all of the drug at once, increasing the risk of side effects. Also, do not split the tablets unless they have a score line and your doctor or pharmacist tells you to do so. Swallow the whole or split tablet without crushing or chewing. The dosage is based on your medical condition, kidney function, and response to treatment. Your doctor may direct you to take a low dose of this medication at first, gradually increasing your dose to lower the chance of side effects such as upset stomach. Your doctor will adjust your dose based on your blood sugar levels to find the best dose for you. Follow your doctor's directions carefully. Take this medication regularly in order to get the most benefit from it. Remember to use it at the same time each day. If you are already taking another anti-diabetic drug (such as chlorpropamide), follow your doctor's directions carefully for stopping/continuing the old drug and starting metformin. Check your blood sugar regularly as directed by your doctor. Keep track of the results, and share them with your doctor. Tell your doctor if your blood sugar measurements are too high or too low. Your dosage/treatment may need to be changed.

SIDE EFFECTS:

Nausea, vomiting, stomach upset, diarrhea, weakness, or a metallic taste in the mouth may occur. If any of these effects persist or worsen, tell your doctor or pharmacist promptly. If stomach symptoms return later (after taking the same dose for several days or weeks), tell your doctor immediately. Stomach symptoms that occur after the first days of your treatment may be signs of lactic acidosis. An empty tablet shell may appear in your stool. This effect is harmless because your body has already absorbed the medication. Remember that your doctor has prescribed this medication because he or she has judged that the benefit to you is greater than the risk of side effects. Many people using this medication do not have serious side effects. Metformin does not usually cause low blood sugar (hypoglycemia). Low blood sugar may occur if this drug is prescribed with other anti-diabetic medications. Talk with your doctor or pharmacist about whether the dose of your other diabetic medication(s) needs to be lowered. Symptoms of low blood sugar include sudden sweating, shaking, fast heartbeat, hunger, blurred vision, dizziness, or tingling hands/feet. It is a good habit to carry glucose tablets or gel to treat low blood sugar. If you don't have these reliable forms of glucose, rapidly raise your blood sugar by eating a quick source of sugar such as table sugar, honey, or candy, or drink fruit juice or non-diet soda. Tell your doctor about the reaction immediately. Low blood sugar is more likely if you drink large amounts of alcohol, do unusually heavy exercise, or do not consume enough calories from food. To help prevent low blood sugar, eat meals on a regular schedule, and do not skip meals. Check with your doctor or pharmacist to find out what you should do if you miss a meal. Symptoms of high blood sugar (hyperglycemia) include thirst, increased urination, confusion, drowsiness, flushing, rapid breathing, and fruity breath odor. If these symptoms occur, tell your doctor immediately. Your doctor may need to adjust your diabetes medication(s). Stop taking this medication and tell your doctor right away if this very serious side effect occurs: lactic acidosis (see Warning section). A very serious allergic reaction to this drug is rare. However, get medical help right away if you notice any of the following symptoms of a serious allergic reaction: rash, itching/swelling (especially of the face/tongue/throat), severe dizziness, trouble breathing. This is not a complete list of possible side effects. If you notice other effects not listed above, contact your doctor or pharmacist. In the US - Call your doctor for medical advice about side effects. You may report side effects to FDA at 1-800-FDA-1088. In Canada - Call your doctor for medical advice about side effects. You may report side effects to Health Canada at 1-866-234-2345.

PRECAUTIONS:

See also Warning section. Before taking this medication, tell your doctor or pharmacist if you are allergic to metformin; or if you have any other allergies. This product may contain inactive ingredients, which can cause allergic reactions or other problems. Talk to your pharmacist for more details. Before using this medication, tell your doctor or pharmacist your medical history, especially of: severe breathing problems (such as obstructive lung disease, severe asthma), metabolic acidosis (such as diabetic ketoacidosis), blood problems (such as anemia, vitamin B12 deficiency), kidney disease, liver disease. Before having surgery or any X-ray/scanning procedure using injectable iodinated contrast material, tell your doctor that you are taking this medication. You will need to temporarily stop this medication before the time of your surgery/procedure. Consult your doctor for further instructions. Before having surgery, tell your doctor or dentist about all the products you use (including prescription drugs, nonprescription drugs, and herbal products). You may experience blurred vision, dizziness, or drowsiness due to extremely low or high blood sugar levels. Do not drive, use machinery, or do any activity that requires alertness or clear vision until you are sure you can perform such activities safely. Limit alcohol while using this medication because it can increase your risk of lactic acidosis and developing low blood sugar. High fever, "water pills" (diuretics such as hydrochlorothiazide), too much sweating, diarrhea, or vomiting may cause loss of too much body water (dehydration) and increase your risk of lactic acidosis. Stop taking this medication and tell your doctor right away if you have prolonged diarrhea or vomiting. Be sure to drink enough fluids to prevent dehydration unless your doctor directs you otherwise. It may be harder to control your blood sugar when your body is stressed (such as due to fever, infection, injury, or surgery). Consult your doctor because increased stress may require a change in your treatment plan, medications, or blood sugar testing. Older adults may be a greater risk for side effects such as low blood sugar or lactic acidosis. During pregnancy, this medication should be used only when clearly needed. Discuss the risks and benefits with your doctor. Your doctor may direct you to use insulin instead of this product during your pregnancy. Follow your doctor's instructions carefully. Metformin can cause changes in the menstrual cycle (promote ovulation) and increase the risk of becoming pregnant. Consult your doctor or pharmacist about the use of reliable birth control while using this medication. Metformin passes into breast milk in small amounts. Consult your doctor before breast-feeding.

DRUG INTERACTIONS:

Drug interactions may change how your medications work or increase your risk for serious side effects. This document does not contain all possible drug interactions. Keep a list of all the products you use (including prescription/nonprescription drugs and herbal products) and share it with your doctor and pharmacist. Do not start, stop, or change the dosage of any medicines without your doctor's approval. Many drugs can affect your blood sugar levels, making it more difficult to control your blood sugar. Before you start, stop, or change any medication, talk with your doctor or pharmacist about how the medication may affect your blood sugar. Check your blood sugar levels regularly as directed by your doctor. Tell your doctor about the results and of any symptoms of high or low blood sugar. (See also Side Effects section.) Your doctor may need to adjust your anti-diabetic medication, exercise program, or diet.

OVERDOSE:

If overdose is suspected, contact a poison control center or emergency room immediately. US residents can call the US National Poison Hotline at 1-800-222-1222. Canada residents can call a provincial poison control center. Overdose can cause lactic acidosis. Symptoms of overdose may include: severe drowsiness, severe nausea/vomiting/diarrhea, rapid breathing, slow/irregular heartbeat.

NOTES:

Do not share this medication with others. You should attend a diabetes education program to learn more about diabetes and all the important aspects of its treatment, including meals/diet, exercise, personal hygiene, medications, and getting regular eye/foot/medical exams. Keep all medical appointments. Laboratory and/or medical tests (such as liver/kidney function tests, blood glucose, hemoglobin A1c, complete blood counts) should be performed periodically to check for side effects and monitor your response to treatment. Check your blood sugar levels regularly as directed.

MISSED DOSE:

If you miss a dose, take it as soon as you remember. If it is near the time of the next dose, skip the missed dose and resume your usual dosing schedule. Do not double the dose to catch up.

STORAGE:

Store at room temperature away from light and moisture. Do not store in the bathroom. Keep all medications away from children and pets. Do not flush medications down the toilet or pour them into a drain unless instructed to do so. Properly discard this product when it is expired or no longer needed. Consult your pharmacist or local waste disposal company for more details about how to safely discard your product.

MEDICAL ALERT:

Your condition can cause complications in a medical emergency. For information about enrolling in MedicAlert, call 1-800-854-1166 (US) or 1-800-668-1507 (Canada).

Manufactured by Tagi Pharamaceuticals

Distributed by: Calvin Scott & Co., Inc. Albuquerque, NM 87123. (800)-545-6545

Information last revised March 2012. Copyright(c) 2012 First Databank, Inc.